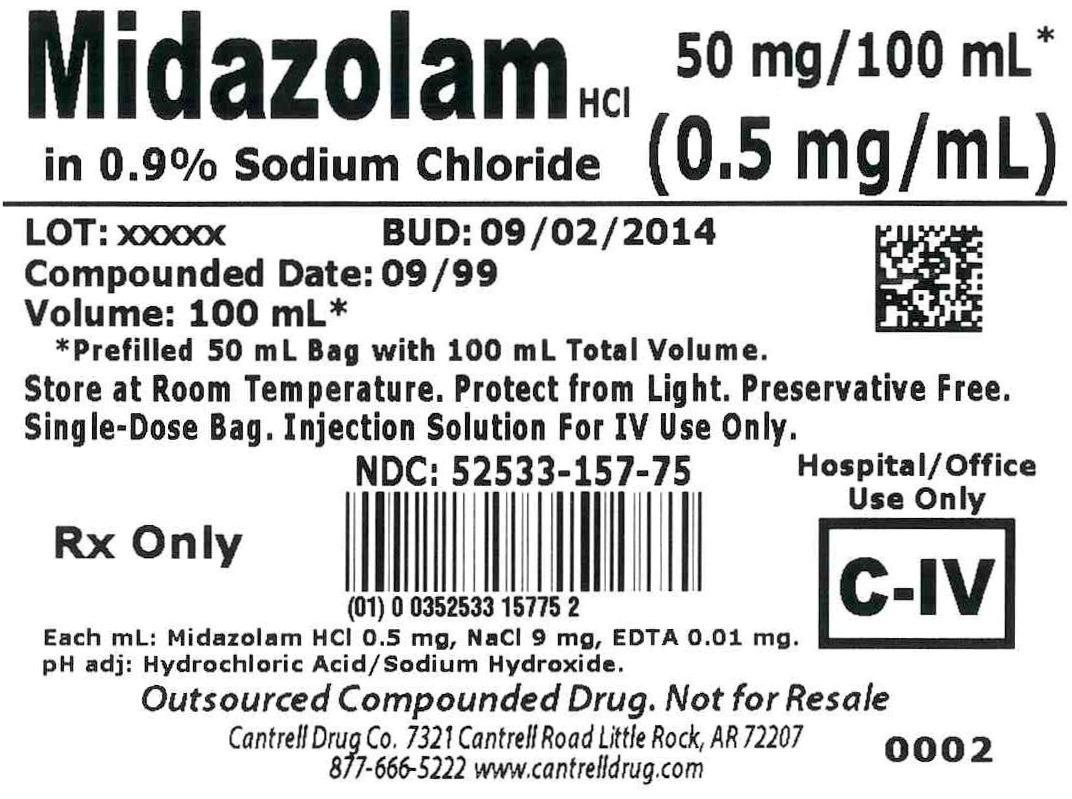 DRUG LABEL: Midazolam HCl
NDC: 52533-157 | Form: INJECTION, SOLUTION
Manufacturer: Cantrell Drug Company
Category: prescription | Type: HUMAN PRESCRIPTION DRUG LABEL
Date: 20150112
DEA Schedule: CIV

ACTIVE INGREDIENTS: MIDAZOLAM HYDROCHLORIDE 0.5 mg/1 mL
INACTIVE INGREDIENTS: Sodium Chloride 9 mg/1 mL; EDETATE DISODIUM 0.01 mg/1 mL; WATER

Midazolam HCl 0.5 mg/mL in 0.9% Sodium Chloride 100 mL Bag